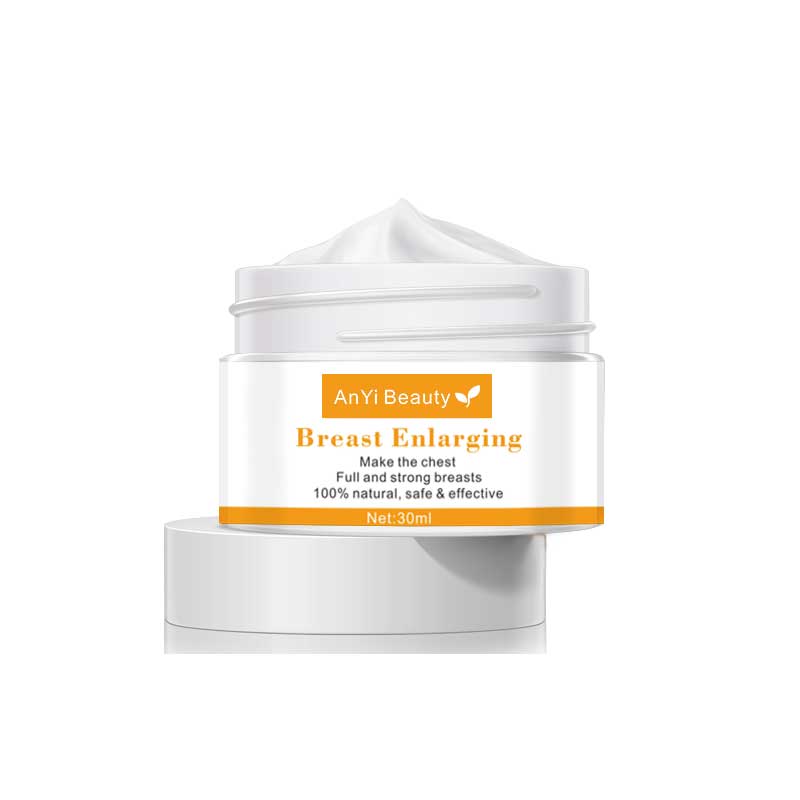 DRUG LABEL: AnYi Beauty Breast Enlarging Cream
NDC: 84037-0106 | Form: CREAM
Manufacturer: Guangzhou Zhicunxiu Cosmetics Co., Ltd
Category: otc | Type: HUMAN OTC DRUG LABEL
Date: 20240823

ACTIVE INGREDIENTS: NIACINAMIDE 5 g/100 mL
INACTIVE INGREDIENTS: SUNFLOWER OIL; POTASSIUM SORBATE; TRIDECETH-6; XANTHAN GUM; ALOE VERA LEAF; WATER; CITRIC ACID MONOHYDRATE; 3-O-ETHYL ASCORBIC ACID; ALPHA-ARBUTIN; PHENOXYETHANOL; GREEN TEA LEAF; TOCOPHEROL; GLYCERIN; GLYCYRRHIZA GLABRA; MORUS ALBA ROOT; CAPRYLYL CAPRYLATE/CAPRATE; GELATIN HYDROLYSATE (PORCINE SKIN, MW 3000); HYALURONIC ACID; TETRAPEPTIDE-21

AnYi Beauty Breast Enlarging Cream

Active Ingredient

Niacinamide 5%

Purpose

Dark Spot Corrector

Warnings

WARNINGS:Keep out of reach of children. For external use only. Before using, test for sensitivity on a small area of skin.

Do not use on damaged skin. Use only as directed. Avoid contact with eyes. Rinse with warm water to remove. Stop use and consult your physician if rash occurs. Do not ingest. If swallowed, get medical help or contact a Poison Control Center right away! Do not use if safety sealis broken or missing. Store in a cool, dry place.

Keep Oot Of Reach Of Children

Keep out of reach of children

Directions

Cleanse the application area and pat dry. Gently massage a thin layer into the affected area of skin until fully absorbed. Protect treated skin from sunlight by following up with an SPF 30+ sunscreen.

Inactive ingredients

Water, Sunflower Oil, Caprylyl Caprylate/Caprate,Glycerin,Trideceth-6, Aloe Vera, Niacinamide, Glycyrrhiza Glabra Extract, Morus Alba Root Extract, Hydrolyzed Oat Protein,Ethyl Ascorbic Acid, Alpha Arbutin, Hyaluronic Acid, Phenoxyethanol,Green Tea Extract, Tetrapeptide-21, Potassium Sorbate, Citric Acid,Xanthan Gum, Tocopherol, Soy Isoflavones, Cistus Ladaniferus Oil,Lemon Essential Oil.

Use

Remove dark spots on face.